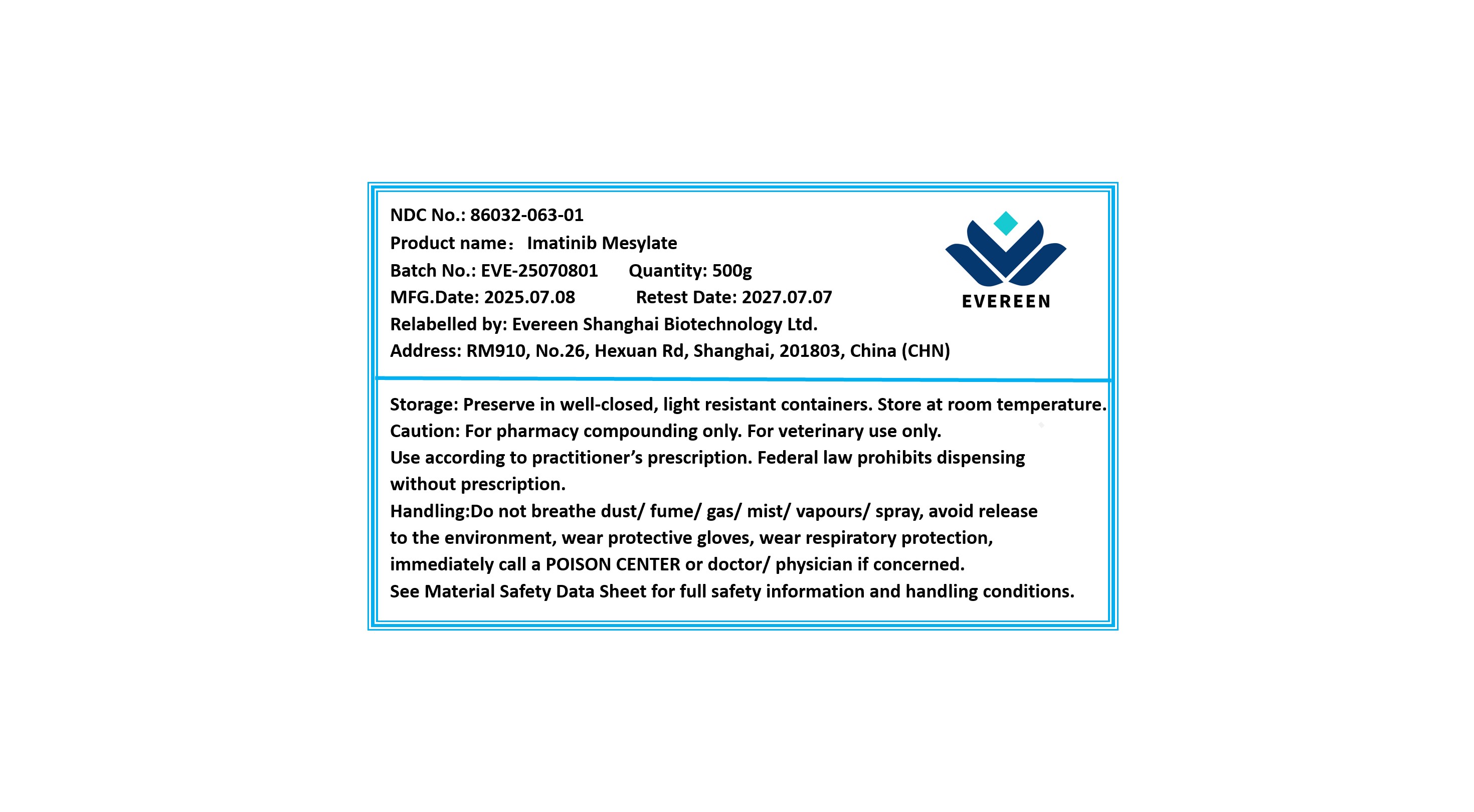 DRUG LABEL: Imatinib Mesylate
NDC: 86032-063 | Form: POWDER
Manufacturer: Evereen Shanghai Biotechnology Ltd.
Category: other | Type: BULK INGREDIENT - ANIMAL DRUG
Date: 20251016

ACTIVE INGREDIENTS: IMATINIB MESYLATE 1 g/1 g

Imatinib Mesylate